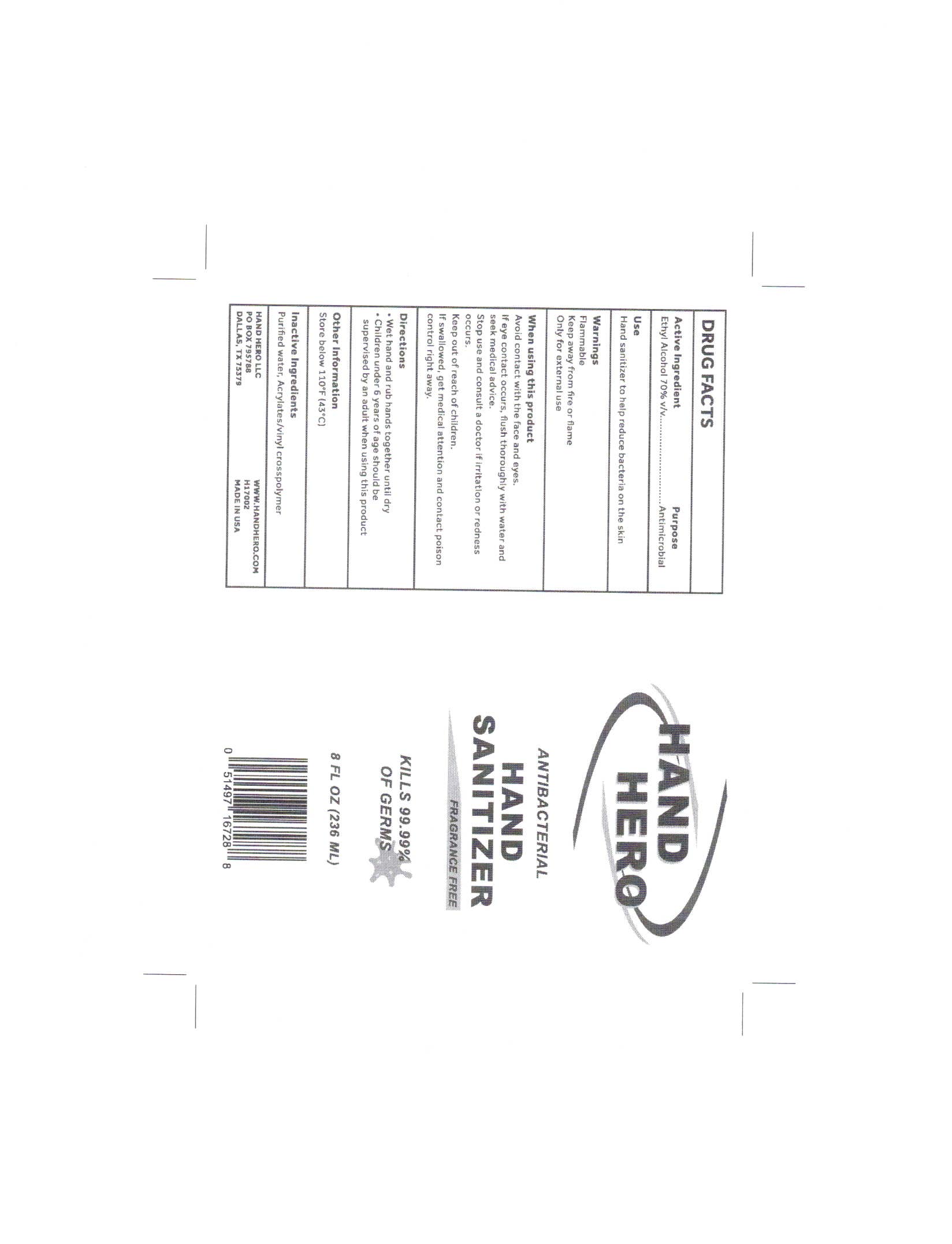 DRUG LABEL: Hand Hero Hand Sanitizer
NDC: 79458-000 | Form: GEL
Manufacturer: Natural Technology, LLC
Category: otc | Type: HUMAN OTC DRUG LABEL
Date: 20220117

ACTIVE INGREDIENTS: ALCOHOL 72 mL/100 mL
INACTIVE INGREDIENTS: RAPIDGEL EZ1 5 mL/100 mL; WATER

Ethyl Alcohol 70% v/v. Purpose: Antimicrobial

236 ml NDC: 79458-000-01

Purpose: Antimicrobial

236ml NDC:79458-000-01

Hand sanitizer to help reduce bacteria on the skin

236ml NDC: 79458-000-01

Flammable Keep away from fire or flame Only for external use

236ml NDC: 79458-000-01

Avoid contact with the face and eyes. If eye contact occurs, flush thoroughly with water and seek medical advice. Stop use and consult a doctor if irritation or redness occurs.

236ml NDC: 79458-000-01

Keep out of reach of children. If swallowed, get medical attention and contact poison control right away.

236ml NDC:79458-000-01

Wet hand and rub hands together until dry Children under 6 years of age should be supervised by an adult when using this product

236ml NDC:79458-000-01

Store below 110^0 F (43^0C)

236ml NDC:79458-000-001

Purified water, Acrylates/vinyl crosspolymer

236ml NDC:79458-000-01

Antibacterial Hand Sanitizer

236 ml NDC: 79458-000-01